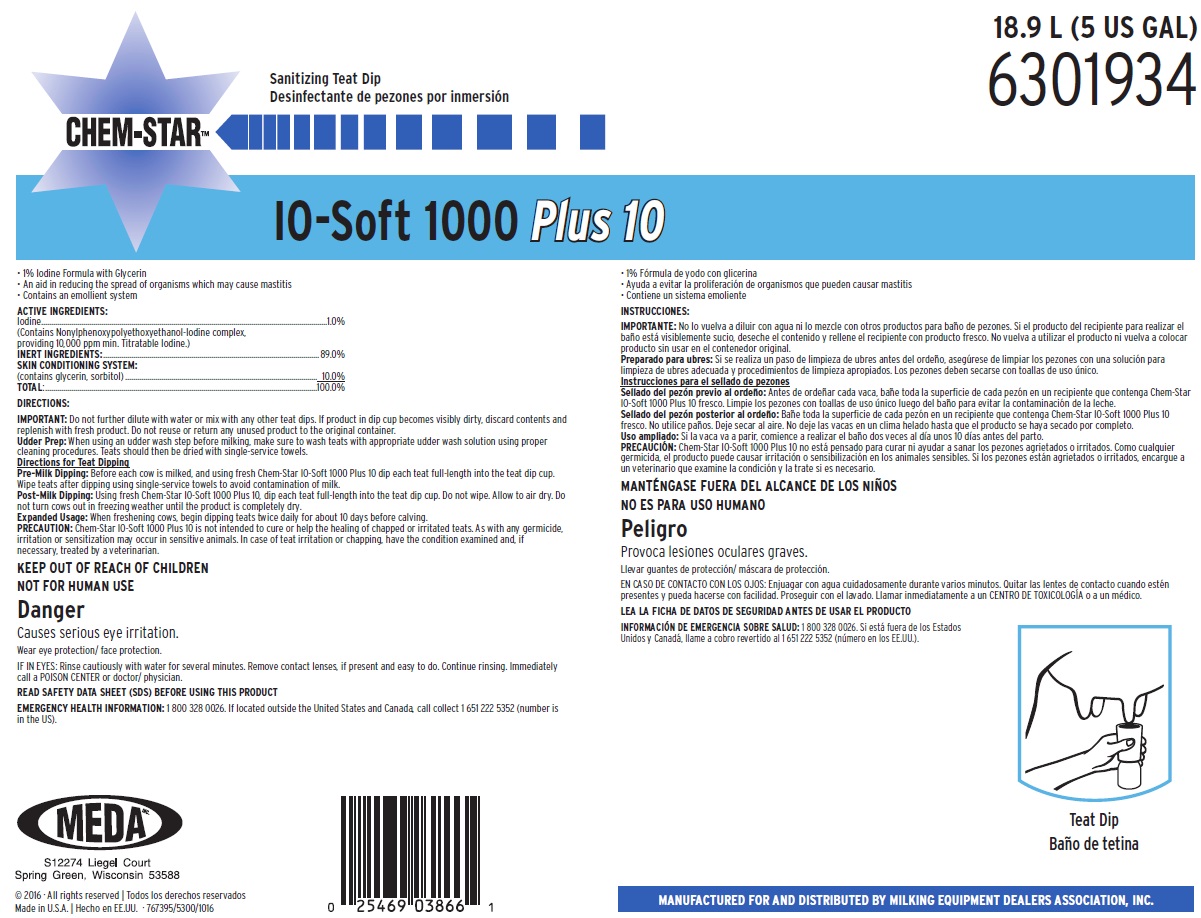 DRUG LABEL: Chem-Star IO-Soft 1000 Plus 10
NDC: 59511-210 | Form: SOLUTION
Manufacturer: MEDA Inc.
Category: animal | Type: OTC ANIMAL DRUG LABEL
Date: 20191022

ACTIVE INGREDIENTS: IODINE 10 mg/1 mL
INACTIVE INGREDIENTS: SORBITOL; GLYCERIN; WATER

KEEP OUT OF REACH OF CHILDREN

NOT FOR HUMAN USE

DANGER

Causes serious eye irritation.

Wear eye protectin/ face protection.

IF IN EYES: Rinse cautiously with water for several minutes. Remove contact lenses, if present and easy to do. Continue rinsing. Immediately call a POISON CENTER or doctor/ physician.

DIRECTIONS:

IMPORTANT: Do not further dilute with water or mix with any other teat dips. If product in dip cup becomes visibly dirty, discard contents and replenish with fresh product. Do not reuse or return any unused product to the original container.

Udder Prep: When using an udder wash step before milking, make sure to wash teats with appropriate udder wash solution using proper cleaning procedures. Teats should then be dried with single-service towels.

Directions for Teat Dipping

Pre-Milk Dipping: Before each cow is milked, and using fresh Chem-Star IO-Soft 1000 Plus 10 dip each teat full-length into the teat dip cup. Wipe teats after dipping using single-service towels to avoid contamination of milk.

Post-Milk Dipping: Using fresh Chem-Star IO-Soft 1000 Plus 10, dip each teat full-length into the teat dip cup. Do not wipe. Allow to air dry. Do not turn cows out in freezing weather until the product is completely dry.

Expanded Usage: When freshening cows, begin dipping teats twice daily for about 10 days before calving.

PRECAUTION: Chem-Star IO-Soft 1000 Plus 10 is not intended to cure or help the healing of chapped or irritated teats. As with any germicide, irritation or sensitization may occur in sensitive animals. In case of teat irritation or chapping, have the condition examined and, if necessary, treated by a veterinarian.

OTHER SAFETY INFORMATION

READ SAFETY DATA SHEET (SDS) BEFORE USING THIS PRODUCT

EMERGENCY HEALTH INFORMATION: 1 800 328 0026. If located outside the United States and Canada, call collect 1 651 222 5352 (number is in the US).

Principal Display Panel and Representative Label

18.9 L (5 US GAL)

6301934

Sanitizing Teat Dip

Chem-Star™

IO-Soft 1000 Plus 10

- 1% Iodine Formula with Glycerin
- An Aid in Reducing the Spread of Organisms Which May Cause Mastitis
- Contains an emollient system

ACTIVE INGREDIENTS: Iodine...........................................................................................1.0%

(Contains Nonylphenoxypolyethoxyethanol-Iodine complex,providing 10,000 ppm min. Titratable Iodine.)

INERT INGREDIENTS:...................................................................89.0%

SKIN CONDITIONING SYSTEM:(contains glycerin, sorbitol).............................................................10.0%

TOTAL:.........................................................................................100.0%

MEDA
S12274 Liegel Court
Spring Green, Wisconsin 53588

© 2016 · All rights reserved
Made in U.S.A.
MANUFACTURED FOR AND DISTRIBUTED BY MILKING EQUIPMENT DEALERS ASSOCIATION, INC.